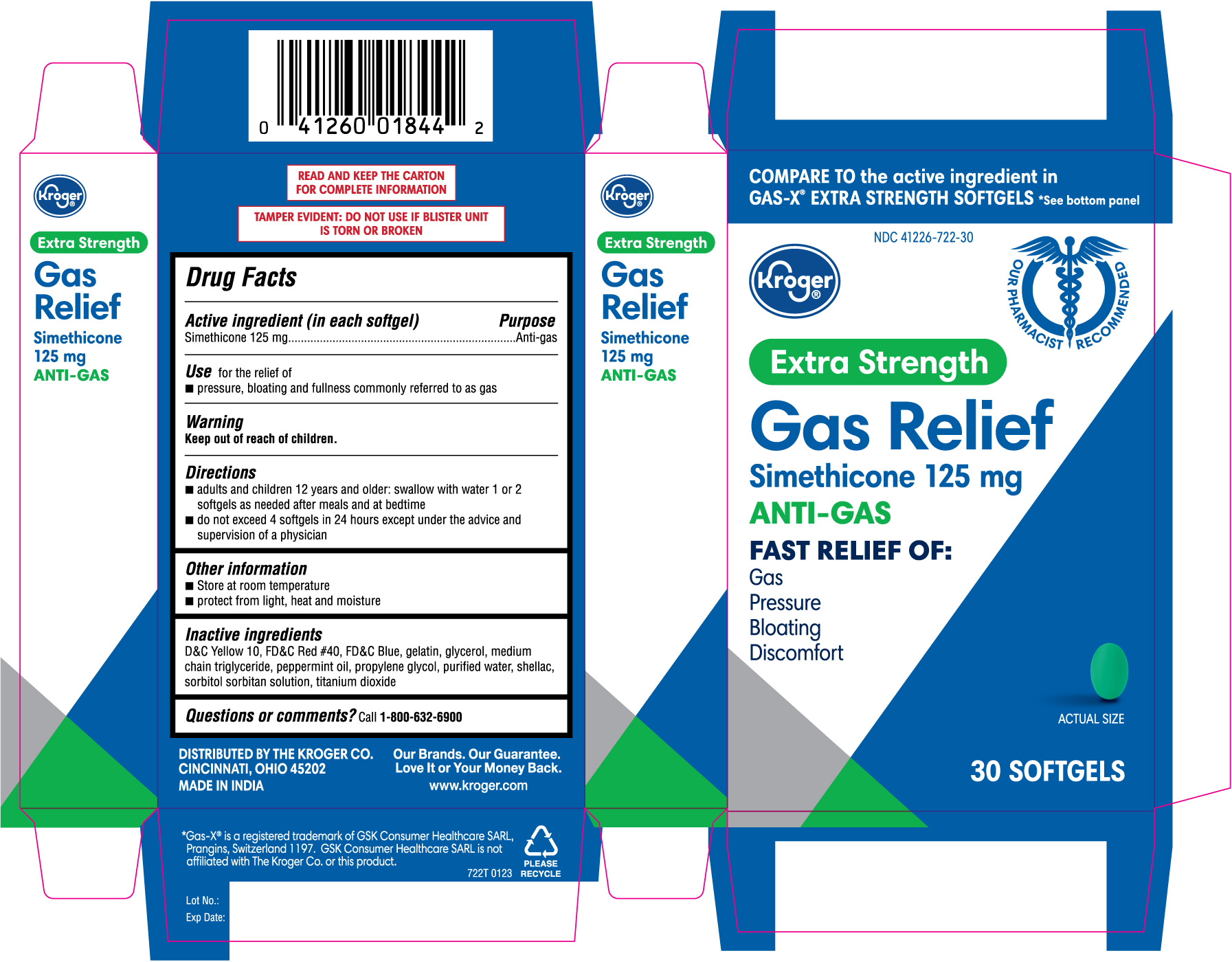 DRUG LABEL: Extra strength gas relief
NDC: 41226-722 | Form: CAPSULE
Manufacturer: KROGER COMPANY
Category: otc | Type: HUMAN OTC DRUG LABEL
Date: 20250211

ACTIVE INGREDIENTS: DIMETHICONE 125 mg/1 1
INACTIVE INGREDIENTS: D&C YELLOW NO. 10; FD&C BLUE NO. 1; MEDIUM-CHAIN TRIGLYCERIDES; PEPPERMINT OIL; PROPYLENE GLYCOL; SHELLAC; SORBITOL SOLUTION; GELATIN; GLYCERIN; WATER; TITANIUM DIOXIDE; FD&C RED NO. 40; SORBITAN

722T_Kroger_41226-722_Simethicone softgel 125mg

Active ingredient

Active ingredient (in each softgel)

Simethicone 125 mg

Purpose

Anti-gas

Use

Use for the relief of

- pressure, bloating and fullness commonly referred to as gas

Warning

Keep out of reach of children.

Directions

- adults and children 12 years and older: swallow with water 1 or 2 softgels as needed after meals and at bedtime
- do not exceed 4 softgels in 24 hours except under the advice and supervision of a physician

Other information

- store at room temperature
- protect from light, heat and moistur e

Inactive ingredients

D&C Yellow 10, FD&C Red #40, FD&C Blue 1, gelatin, glycerol, medium chain triglyceride, peppermint oil, propylene glycol, purified water, shellac, sorbitol sorbitan solution, titanium dioxide

Questions or comments? Call 1-800-632-6900